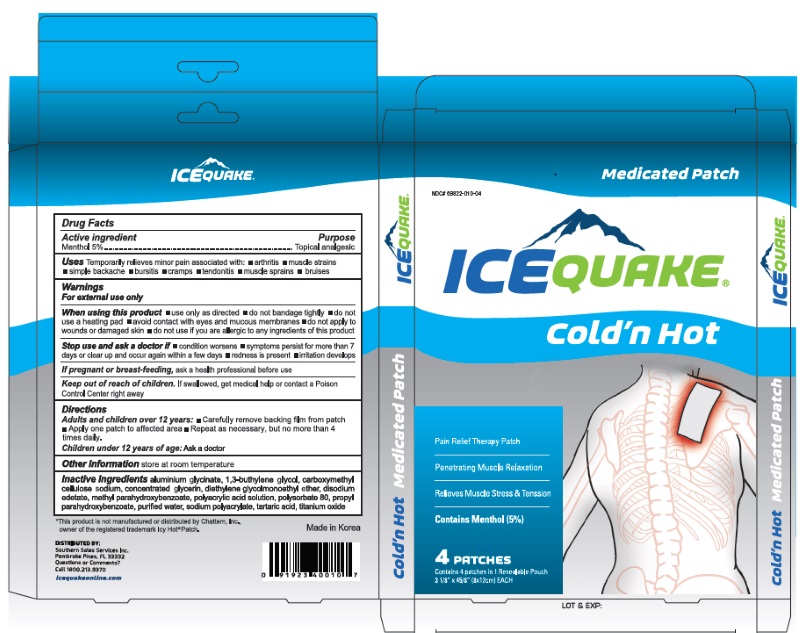 DRUG LABEL: ICEQUAKE Cold Hot
NDC: 69822-010 | Form: PATCH
Manufacturer: Southern Sales & Service, Inc.
Category: otc | Type: HUMAN OTC DRUG LABEL
Date: 20190311

ACTIVE INGREDIENTS: MENTHOL 5 g/100 g
INACTIVE INGREDIENTS: DIHYDROXYALUMINUM AMINOACETATE; BUTYLENE GLYCOL; CARBOXYMETHYLCELLULOSE SODIUM; GLYCERIN; DIETHYLENE GLYCOL; EDETATE DISODIUM ANHYDROUS; METHYLPARABEN; POLYACRYLIC ACID (250000 MW); POLYSORBATE 80; PROPYLPARABEN; WATER; SODIUM POLYACRYLATE (2500000 MW); TARTARIC ACID; TITANIUM DIOXIDE

ICEQUAKE Cold'n Hot

WARNINGS

For External Use Only.

ACTIVE INGREDIENT

Active Ingredient ...............................................................................................Purpose
Menthol 5%...............................................................................................Topical Analgesic

INACTIVE INGREDIENT

Aluminium glycinate,1,3-buthylene Glycol, Carboxymethylcellulose Sodium, Concentrated Glycerin, diethylene Glycolmonoethyl Ether, Disodium Edetate, Methyl Parahydroxybenzoate, Polyacrylic Acid Solution, Polysorbate 80, Propyl Parahydroxybenzoate, Purified Water, Sodium Polyacrylate, Tartaric Acid, Titanium Oxide

INDICATIONS & USAGE

Temporarily relieves minor pain associated with: ■ arthritis ■ simple backache ■ bursitis ■ tendonitis<br />■ muscle strains ■ muscle sprains ■ bruises ■ cramps

DOSAGE & ADMINISTRATION

Adults and children 12 years of age and over: Carefully remove backing from patch.

Apply one patch to affected area

Repeat as necessary, but no more than 4 times daily.

Children under 12 years of age: Ask a doctor.

PURPOSE

Topical Analgesic

When using this product

Use only as directed

■ Do not bandage tightly.

■ Do not use a heating pad.

■ Avoid contact with eyes and mucous membranes.

■ Don’t apply to wounds or damaged skin.

■ Do not use if you are alergic to any ingredients of this product.

Stop use and ask a doctor

■ If condition worsens

■ If symptoms persist for more than 7 days or clear up and occur again within a few days.

■ If redness is present

■ If irritation develops

KEEP OUT OF REACH OF CHILDREN

If swallowed, get medical help or contact a Poison Control Center right away.

If pregnant or breastfeeding

ask a health professional before use.

PACKAGE LABEL

Southern Sales Services Inc
Pembroke Pines, FL 33332